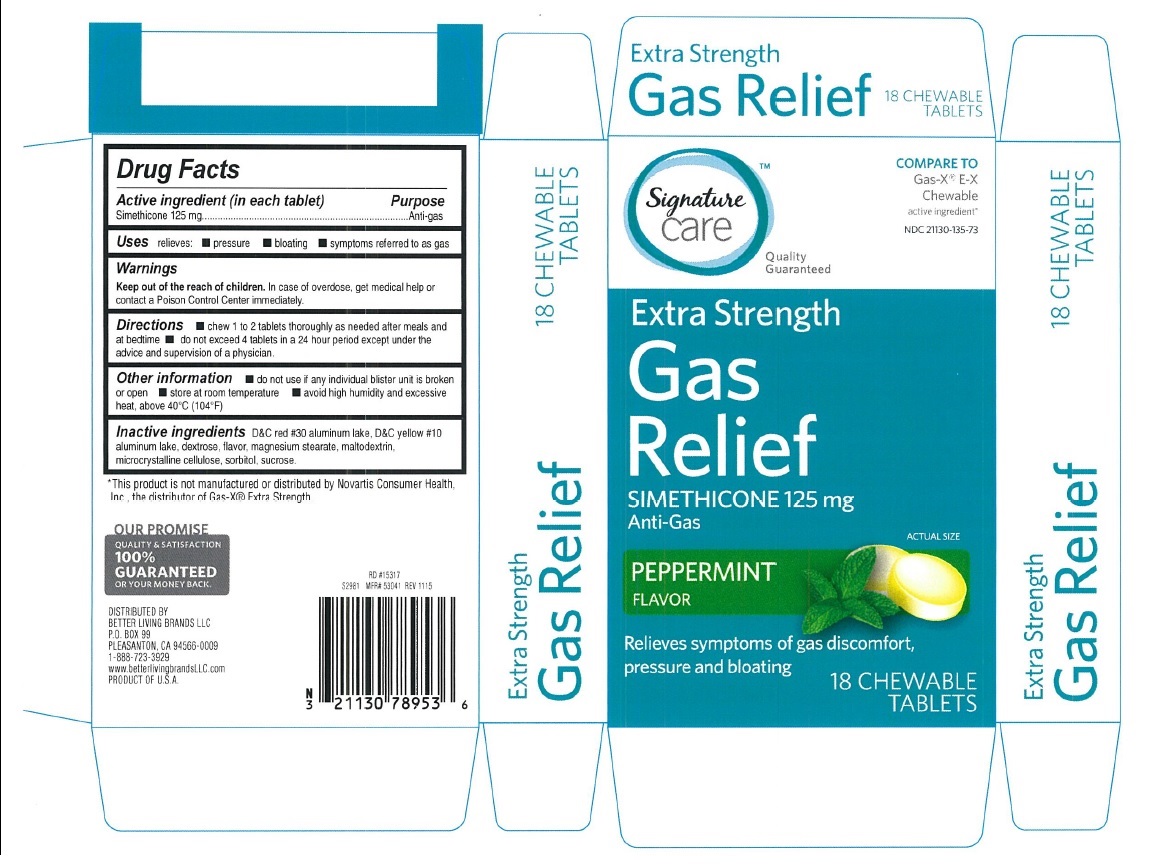 DRUG LABEL: Gas Relief
NDC: 21130-135 | Form: TABLET, CHEWABLE
Manufacturer: Safeway
Category: otc | Type: HUMAN OTC DRUG LABEL
Date: 20160108

ACTIVE INGREDIENTS: DIMETHICONE 125 mg/1 1
INACTIVE INGREDIENTS: D&C RED NO. 30; D&C YELLOW NO. 10; DEXTROSE; MAGNESIUM STEARATE; MALTODEXTRIN; CELLULOSE, MICROCRYSTALLINE; SORBITOL

Extra strength Gas Relief Peppermint Tablets

Active ingredient (in each tablet)

Simethicone 125 mg

Purpose

Anti-gas

Uses

relieves:

- pressure
- bloating
- symptoms referred to as gas

Warnings

Keep out of the reach of children. In case of overdose, get medical help or contact a poison control center immediately.

Directions

- chew 1 to 2 tablets thoroughly as needed after meals and at bedtime
- do not exceed 4 tablets in a 24 hour period except under the advice and supervision of a physician

Other information

- do not use if any individual blister unit is broken or open
- store at room temperature
- avoid high humidity and excessive heat, above 40oC (104oF)

Inactive ingredients

D&C red 30 aluminum lake, D&C yellow 10 aluminum lake, dextrose, flavor, magnesium stearate, maltodextrin, microcrystalline cellulose, sorbitol, sucrose

PDP

*Compare to GAS-X®E-X Chewable active ingredient

Signature Care

Extra strength Gas Relief

Simethicone 125 mg

Anti-Gas

Peppermint Flavor

Relieves symptoms of gas discomfort, pressure and bloating

18 chewable tablets